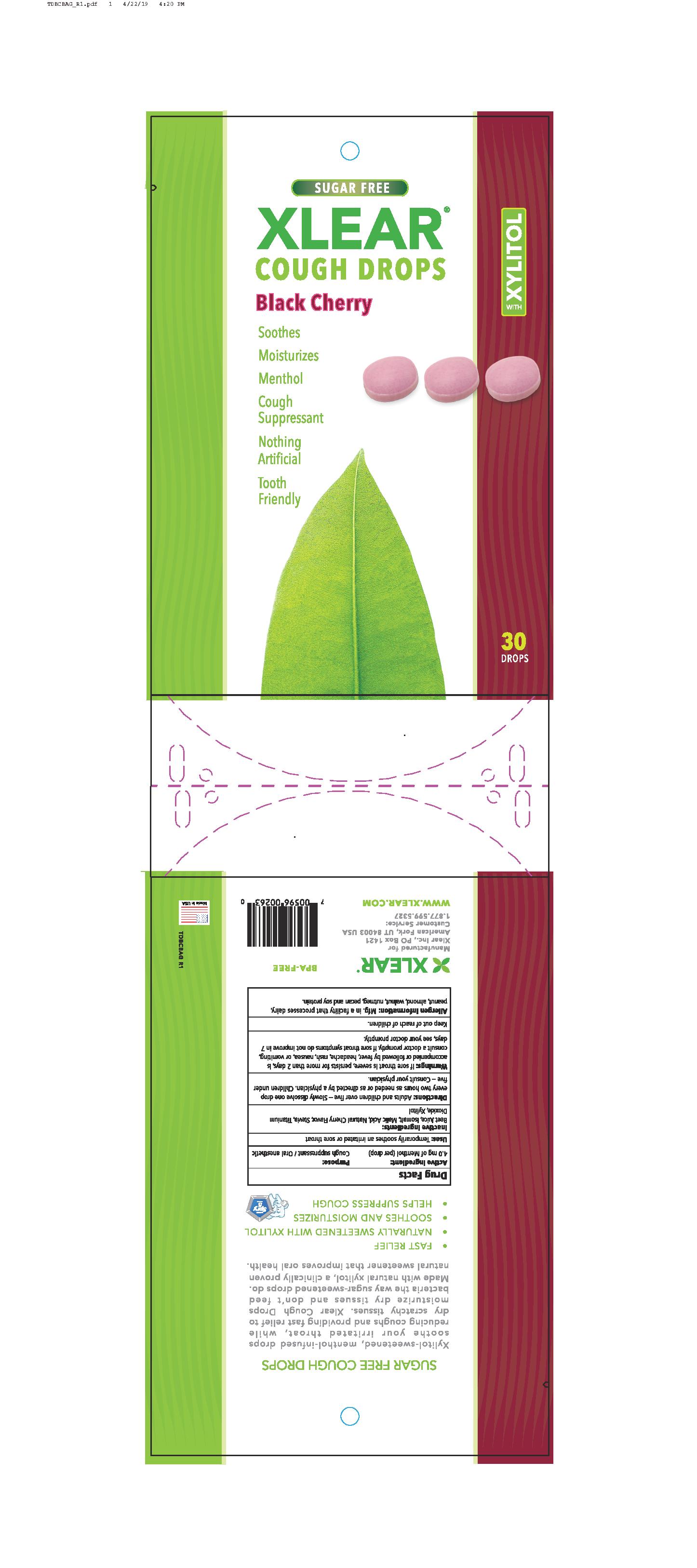 DRUG LABEL: Xlear Cough Drops (Black Cherry)
NDC: 27017-020 | Form: LOZENGE
Manufacturer: Xlear Inc.
Category: otc | Type: HUMAN OTC DRUG LABEL
Date: 20230110

ACTIVE INGREDIENTS: MENTHOL 4 mg/1 1
INACTIVE INGREDIENTS: MALIC ACID; TITANIUM DIOXIDE; BEET JUICE; XYLITOL; STEVIA LEAF; ISOMALT

Xlear Cough Drops (Black Cherry)

ACTIVE INGREDIENT

4.0 mg of menthol (per drop)

PURPOSE

Cough Suppressant / Oral Anesthetic

INDICATIONS AND USAGE

Temporarily soothes an irritated or sore throat

INACTIVE INGREDIENT

Bett Juice, Isomalt, Malic Acid, Natural Cherry Flavor, Stevia, Titanium Dioxide, Xylitol

DOSAGE AND ADMINISTRATION

Adults and children over five - Slowly dissolve one drop every two hours as needed or as directed by a physician. Children under five - Consult your physician.

WARNINGS

If sore throat is severe, persists for more than 2days, is accompanied or followed by fever, headache, rash, nausea, or vomiting, consult a doctor promptly. If sore throat symptoms do not improve in 7 days, see your doctor promptly.

Keep out of reach of children.

OTHER SAFETY INFORMATION

Allergen Information: Mfg. in a facility that processes dairy, peanut, almond, walmut, nutmeg, pecan and soy protein.